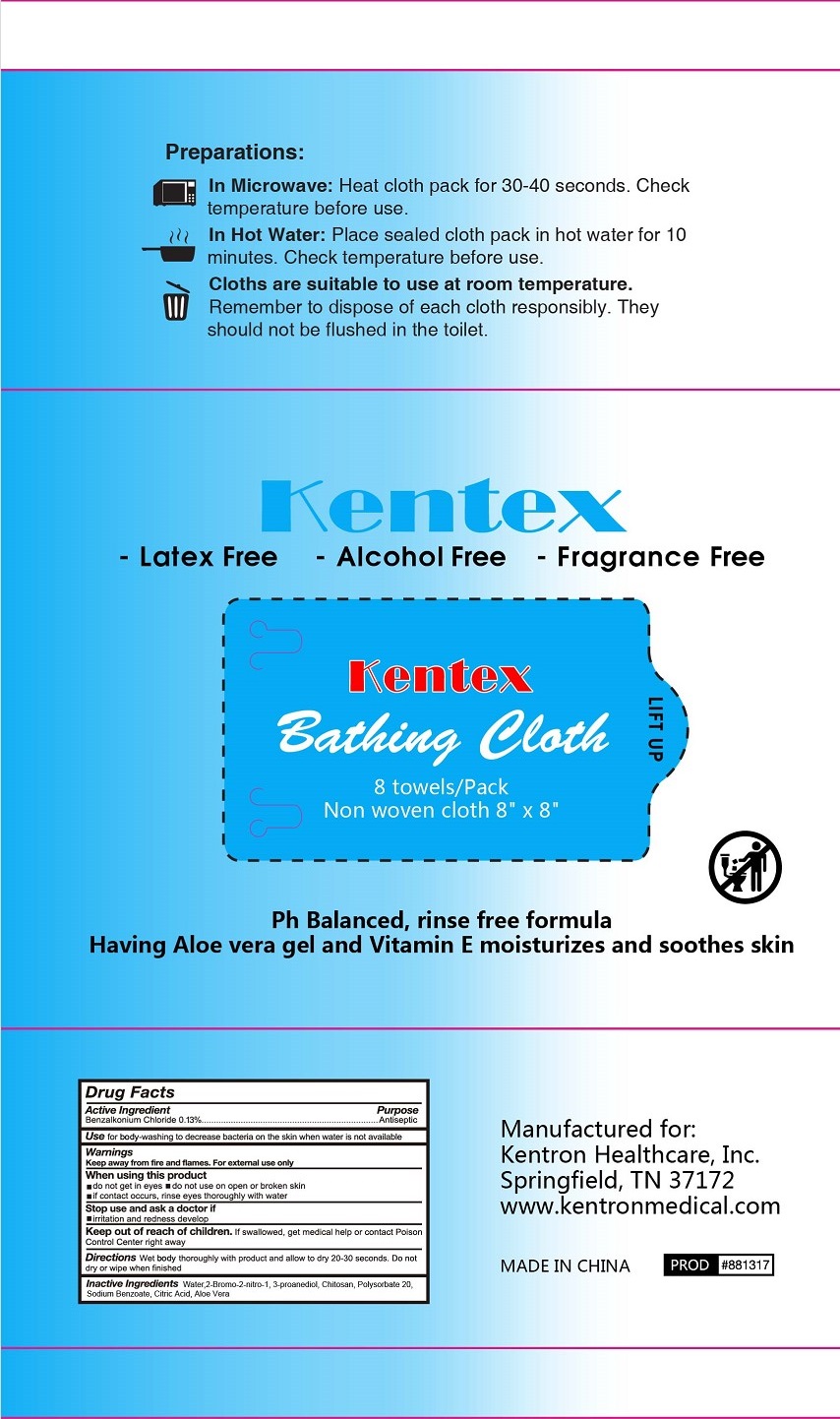 DRUG LABEL: Kentex Bathing Cloth
NDC: 77435-301 | Form: CLOTH
Manufacturer: HAINING LILY CLEANING PRODUCTS CO., LTD
Category: otc | Type: HUMAN OTC DRUG LABEL
Date: 20240310

ACTIVE INGREDIENTS: BENZALKONIUM CHLORIDE 0.13 g/100 g
INACTIVE INGREDIENTS: WATER; POLYSORBATE 20; SODIUM BENZOATE; ACETYLTRIETHYL CITRATE; ALOE VERA LEAF

Kentex Bathing Cloth

Active Ingredient

BENZALKONIUM CHLORIDE .......... 0.13%

Purpose

Antiseptic

USE

For body-washng to decrease bacteria on the skin when water is not available

Warning

- For external use only.
- When using this product, do not get in eyes; do not use on open or broken skin, if contact occurs, rinse eyes throughly with water

- Stop use and ask a doctor, if irritaion and redness develop

KEEP OUT OF REACH OF CHILDREN

●If swallowed, get medical help or contact a Poison Control Center right away.

Directions

Wet body thoroughly with product and allow o dry 20-30 seconds. Do no dry or wipe when finished

Inactive ingredients

water, 2-bromo-2-nitro-1, 3-pproanediol, Chitosan Polysorbate 20, Sodium Bezoate, Citric Acid, Aloe Vera